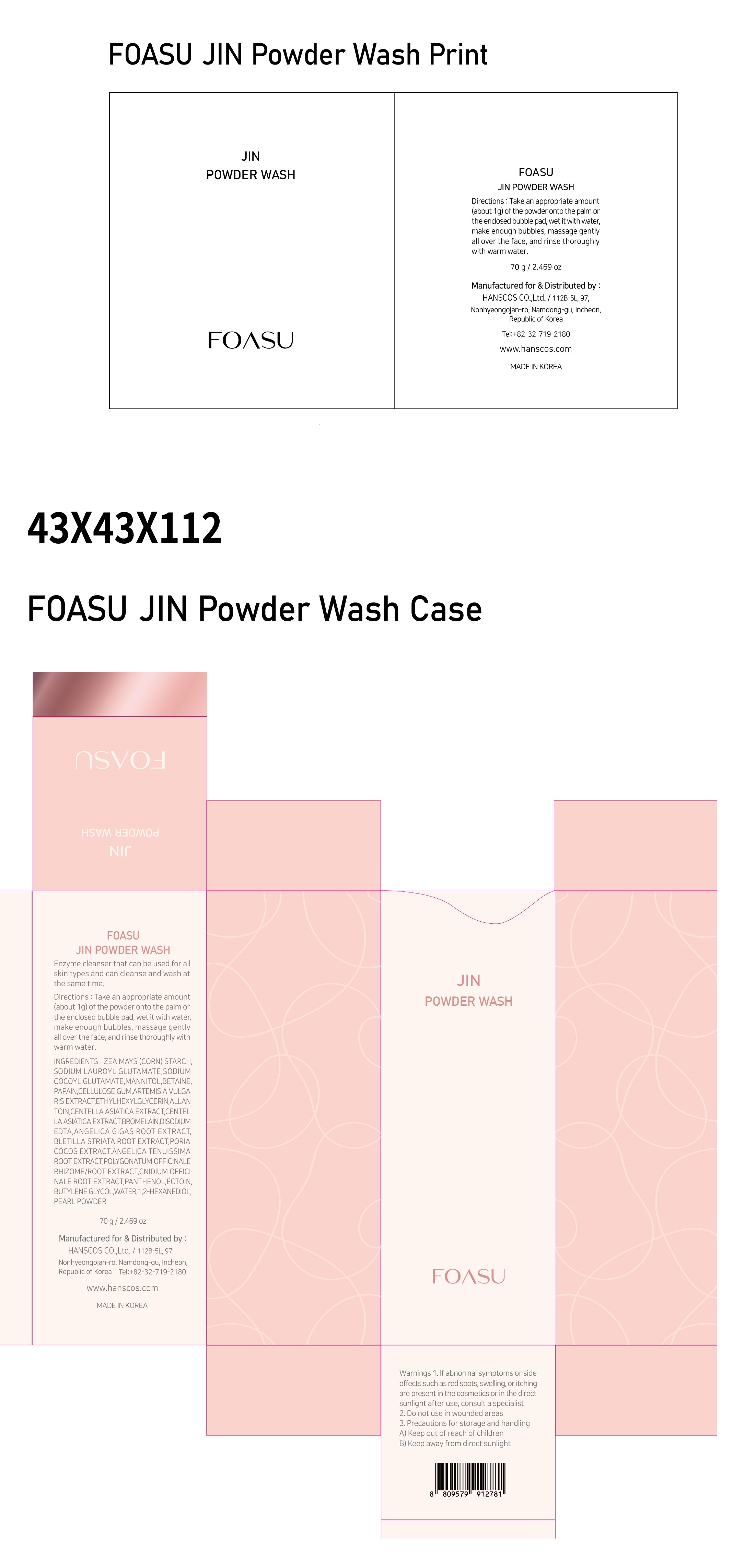 DRUG LABEL: FOASU JIN POWDERWASH
NDC: 77964-005 | Form: POWDER
Manufacturer: HANSCOS Co.,Ltd.
Category: otc | Type: HUMAN OTC DRUG LABEL
Date: 20220227

ACTIVE INGREDIENTS: ALLANTOIN 0.1 g/100 g; PANTHENOL 0.01 g/100 g
INACTIVE INGREDIENTS: WATER; BUTYLENE GLYCOL

Active ingredient

allantoin, panthenol

Purpose

skin protectant

Use

apply proper amount to the skin, or the enclosed bubble pad, wet it with water, make enough bubbles, massage gently all over the face, and rinse thoroughly with warm water

Warnings

For external use only

1) Please consult your doctor if you experience side effects such as swelling, itching, or reddening on the area where you applied this product

2) Do not apply on wounds or cuts. 3) Do not store where children may reach, and avoid keeping it exposed to direct sunlight.

Directions

for external use only

Inactive ingredients

ZEA MAYS (CORN) STARCH
SODIUM LAUROYL GLUTAMATE
SODIUM COCOYL GLUTAMATE
MANNITOL
BETAINE
PAPAIN
CELLULOSE GUM
ARTEMISIA VULGARIS EXTRACT
ETHYLHEXYLGLYCERIN
CENTELLA ASIATICA EXTRACT
CENTELLA ASIATICA EXTRACT
BROMELAIN
DISODIUM EDTA
ANGELICA GIGAS ROOT EXTRACT
BLETILLA STRIATA ROOT EXTRACT
PORIA COCOS EXTRACT
ANGELICA TENUISSIMA ROOT EXTRACT
POLYGONATUM OFFICINALE RHIZOME/ROOT EXTRACT
CNIDIUM OFFICINALE ROOT EXTRACT
ECTOIN
BUTYLENE GLYCOL
WATER
1,2-HEXANEDIOL
PEARL POWDER

Keep out of reach of children. If swallowed, get medical help or contact a Poison Control Center right away.